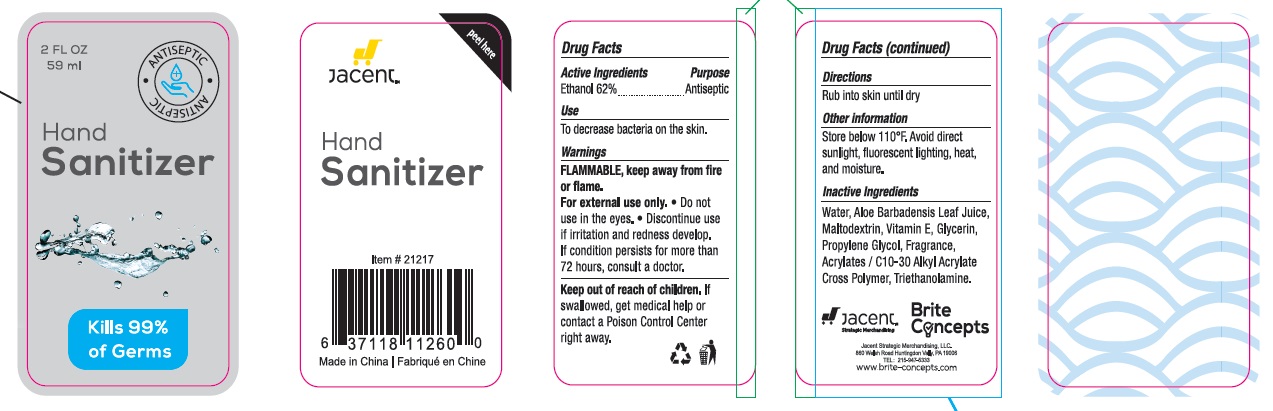 DRUG LABEL: Hand Sanitizer
NDC: 73326-001 | Form: GEL
Manufacturer: Jacent Strategic Merchandising, LLC.
Category: otc | Type: HUMAN OTC DRUG LABEL
Date: 20190827

ACTIVE INGREDIENTS: ALCOHOL 62 mL/100 mL
INACTIVE INGREDIENTS: .ALPHA.-TOCOPHEROL; MALTODEXTRIN; ALOE VERA LEAF; WATER; GLYCERIN; PROPYLENE GLYCOL; CARBOMER COPOLYMER TYPE A (ALLYL PENTAERYTHRITOL CROSSLINKED); TROLAMINE

Active Ingredients:
Ethanol 62%

Purpose

Antiseptic

Use

To decrease bacteria on the skin .

Warnings

Flammable. Keep away from fire or flame.

For external use only.

Do not use in the eyes.

STOP USE

Discontinue use if irritation or redness develop. If condition persists for more that 72 hours, consult a doctor.

Keep out of reach of children. If swallowed, get medical help or contact a Poison Control Center right away.

Directions

Rub into skin until dry.

Inactive ingredients

Water, Aloe Barbadensis Leaf Juice, Maltodextrin, Vitamin E, Glycerin, Propylene Glycol, Fragrance, Acrylates/C10-C30 alkyl acrylate crosspolymer, Triethanolamine.

Other Information

Store below 110F. Avoid direct sunlight, fluorescent lightning,heat and moisture.